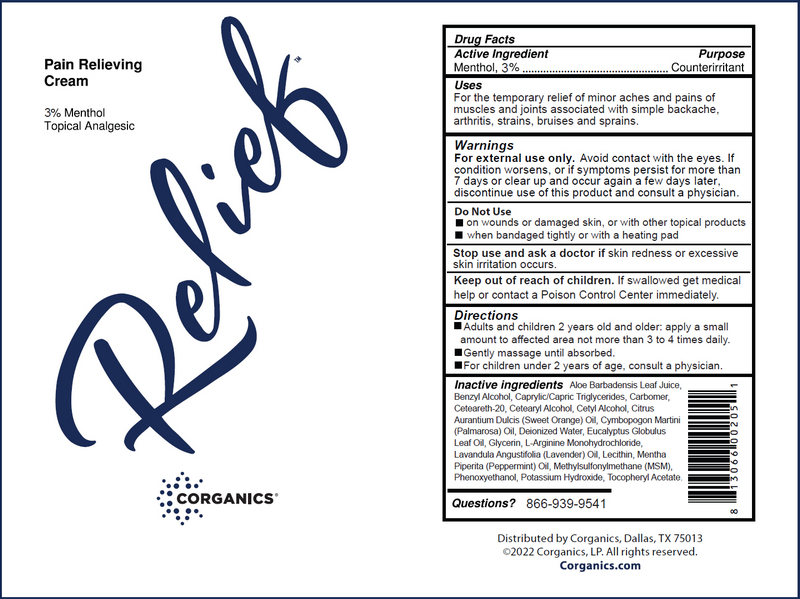 DRUG LABEL: Relief Pain Relieving Cream
NDC: 58559-002 | Form: CREAM
Manufacturer: Corganics, LP
Category: otc | Type: HUMAN OTC DRUG LABEL
Date: 20231026

ACTIVE INGREDIENTS: MENTHOL 3.0 g/100 g
INACTIVE INGREDIENTS: ALOE; BENZYL ALCOHOL; CAPRYLIC/CAPRIC/LAURIC TRIGLYCERIDE; CARBOMER COPOLYMER TYPE A; POLYOXYL 20 CETOSTEARYL ETHER; CETOSTEARYL ALCOHOL; CETYL ALCOHOL; ORANGE OIL; PALMAROSA OIL; WATER; EUCALYPTUS OIL; GLYCERIN; ARGININE; LAVENDER OIL; HYDROGENATED SOYBEAN LECITHIN; DIMETHYL SULFONE; PEPPERMINT OIL; PHENOXYETHANOL; POTASSIUM HYDROXIDE; .ALPHA.-TOCOPHEROL ACETATE

DRUG FACTS

ACTIVE INGREDIENT

Menthol 3%

PURPOSE

Counterirritant

USAGE

For the temporary relief of minor aches and pains of muscles and joints associated with simple backache, arthritis, strains, bruises and sprains.

WARNINGS

For external use only. Avoid contact with the eyes. If condition worsens, or if symptons persist for more than 7 days or clear up and occur again after a few days, discontinue use of this product and consult a physician.

Do Not Use

- on wounds or damaged skin
- when bandaged tightly or with a heating pad
- with other topical products

Keep out of reach of children. If swallowed get medical help or contact a Poison Control Center immediately.

DIRECTIONS

- Adults and children 2 years old and older: apply a small amount to affected area not more than 3 to 4 times daily.
- Gently massage until absorbed.
- Children under 2 years of age: consult a physician.

INACTIVE INGREDIENTS

Aloe Barbadensis Leaf Juice, Benzyl Alcohol, Caprylic/Capric Triglycerides, Carbomer, Ceteareth-20, Cetearyl Alcohol, Cetyl Alcohol, Citrus Aurantium Dulcis (Sweet Orange) Oil, Cymbopogon Martini (Palmarosa) Oil, Deionized Water, Eucalyptus Globulus Leaf Oil, Glycerine, L-Arginine Monohydrochloride, Lavandula Angustifolia (Lavender) Oil, Lecithin, Mentha Piperita (Peppermint Oil), Methylsulfonylmethane, Phenoxyethanol, Potassium Hydroxide, Tocopheryl Acetate